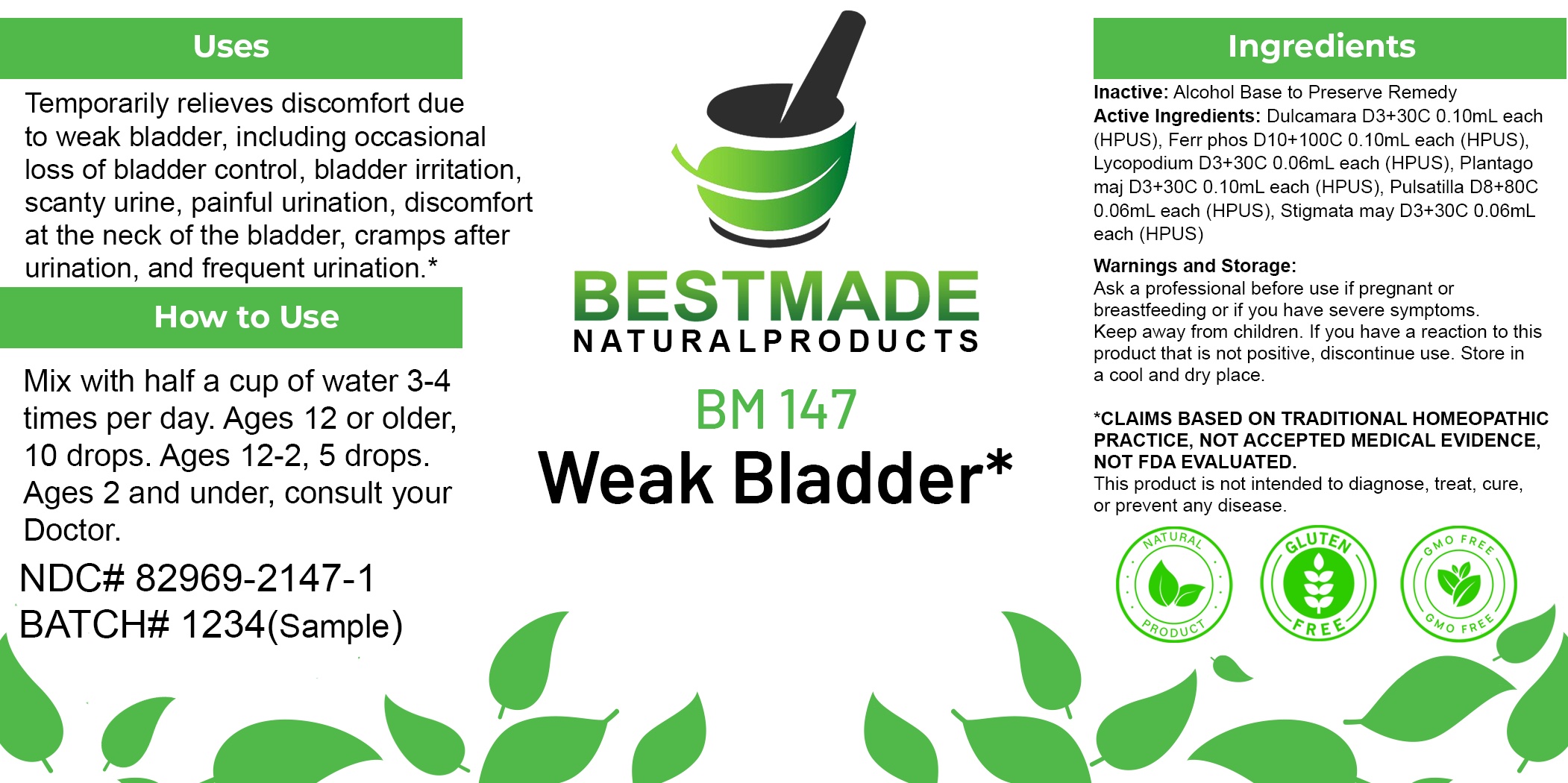 DRUG LABEL: Bestmade Natural Products BM147
NDC: 82969-2147 | Form: LIQUID
Manufacturer: Bestmade Natural Products
Category: homeopathic | Type: HUMAN OTC DRUG LABEL
Date: 20250218

ACTIVE INGREDIENTS: SOLANUM DULCAMARA FLOWER 30 [hp_C]/30 [hp_C]; PULSATILLA PRATENSIS FLOWERING TOP 30 [hp_C]/30 [hp_C]; PLANTAGO MAJOR WHOLE 30 [hp_C]/30 [hp_C]; FERROSOFERRIC PHOSPHATE 30 [hp_C]/30 [hp_C]; LYCOPODIUM CLAVATUM SPORE 30 [hp_C]/30 [hp_C]; CORN SILK 30 [hp_C]/30 [hp_C]
INACTIVE INGREDIENTS: ALCOHOL 30 [hp_C]/30 [hp_C]

BM147

DOSAGE AND ADMINISTRATION

How to Use

Mix with half a cup of water 3-4 times per day. Ages 12 or older, 10 drops. Ages 12-2, 5 drops. Ages 2 and under, consult your Doctor.

Inactive:

Alcohol Base to Preserve Product

ACTIVE INGREDIENTS

Dulcamara D3+30C 0.10mL each (HPUS), Ferr phos D10+100C 0.10mL each (HPUS), Lycopodium D3+30C 0.06mL each (HPUS), Plantago maj D3+30C 0.10mL each (HPUS), Pulsatilla D8+80C 0.06mL each (HPUS), Stigmata may D3+30C 0.06mL each (HPUS)

Uses
Temporarily relieves discomfort due to weak bladder, including occasional loss of bladder control, bladder irritation, scanty urine, painful urination, discomfort at the neck of the bladder, cramps after urination, and frequent urination.*

Uses
Temporarily relieves discomfort due to weak bladder, including occasional loss of bladder control, bladder irritation, scanty urine, painful urination, discomfort at the neck of the bladder, cramps after urination, and frequent urination.*

KEEP OUT OF REACH OF CHILDREN

Warnings and Storage:

Ask a professional before use if pregnant or breastfeeding or if you have severe symptoms.

Keep away from children. If you have a reaction to this product that is not positive, discontinue use. Store in a cool and dry place

*CLAIMS BASED ON TRADITIONAL HOMEOPATHIC PRACTICE, NOT ACCEPTED MEDICAL EVIDENCE NOT FDA EVALUATED.
This product is not intended to diagnose, treat, cure, or prevent any disease.

Warnings and Storage:

Ask a professional before use if pregnant or breastfeeding or if you have severe symptoms.

Keep away from children. If you have a reaction to this product that is not positive, discontinue use. Store in a cool and dry place

*CLAIMS BASED ON TRADITIONAL HOMEOPATHIC PRACTICE, NOT ACCEPTED MEDICAL EVIDENCE NOT FDA EVALUATED.
This product is not intended to diagnose, treat, cure, or prevent any disease.

Entire package label